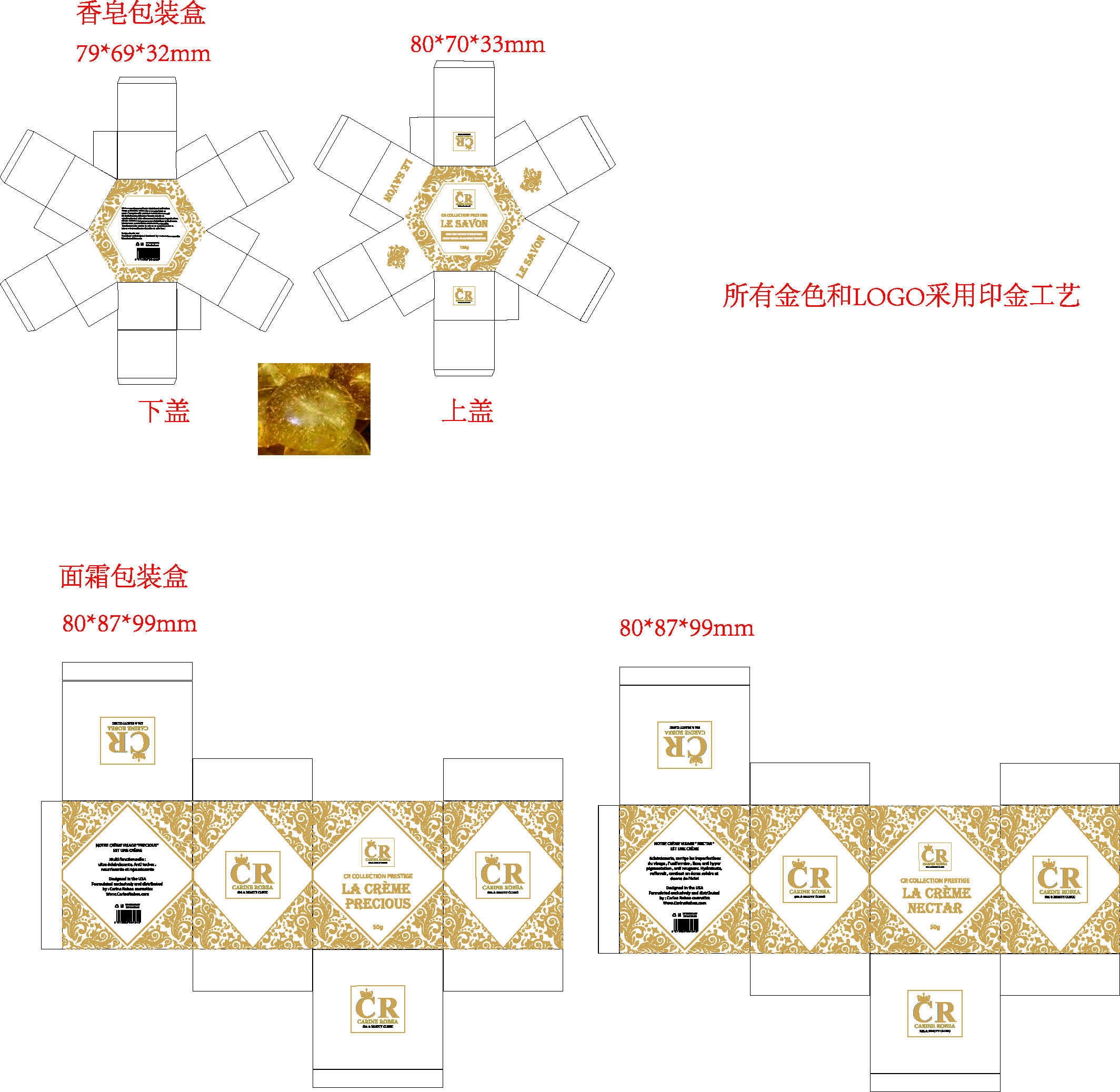 DRUG LABEL: CR whitening Cream
NDC: 84423-083 | Form: CREAM, AUGMENTED
Manufacturer: Guangzhou Kadiya Biotechnology Co., Ltd.
Category: otc | Type: HUMAN OTC DRUG LABEL
Date: 20250716

ACTIVE INGREDIENTS: ARBUTIN 1 g/50 g; NIACINAMIDE 1.5 g/50 g
INACTIVE INGREDIENTS: ALPHA-TOCOPHEROL; AQUA; KOJIC ACID; PHENOXYETHANOL

PURPOSE

For Facial Skin Moisturizing, Antioxidant, Blemish Removal, Whitening, Brightening

INACTIVE INGREDIENT

AQUA
Acide Kojique
Extrait de Réglisse
Vitamin E
Phenoxyethanol

WARNINGS

1. Before use, perform a skin test on your arm and discontinue use if you have allergy symptoms or skin abnormalities.

2、For external use only, avoid contact with eyes when used

3、Keep out of reach of children

INDICATIONS AND USAGE

The cream-based facial cream needs to be warmed and emulsified in the palm of your hand. The emulsified facial cream can be applied directly.

DOSAGE AND ADMINISTRATION

The standard dosage of facial cream is approximately 1 gram (equivalent to the size of 1-2 soybeans). The exact amount may vary depending on skin type, season, and the texture of the product.

KEEP OUT OF REACH OF CHILDREN SECTION

ACTIVE INGREDIENT

Arbutine 2%
Nicotinamide3%
Acide Kojique0.8%

PACKAGE LABEL

Active Ingredients
Arbutine 2%
Nicotinamide3%
Acide Kojique0.8%
Uses：
For Facial Skin Moisturizing, Antioxidant, Blemish Removal, Whitening, Brightening
The storage method：
Store sealed in a cool place and out of sunlight
Warning.
1.Before use, perform a skin test on your arm and discontinue use if you have allergy symptoms or skin abnormalities.
2、For external use only, avoid contact with eyes when used
3、Keep out of reach of children
AQUA, Acide Kojique, Extrait de Réglisse, Vitamin E, Phenoxyethanol